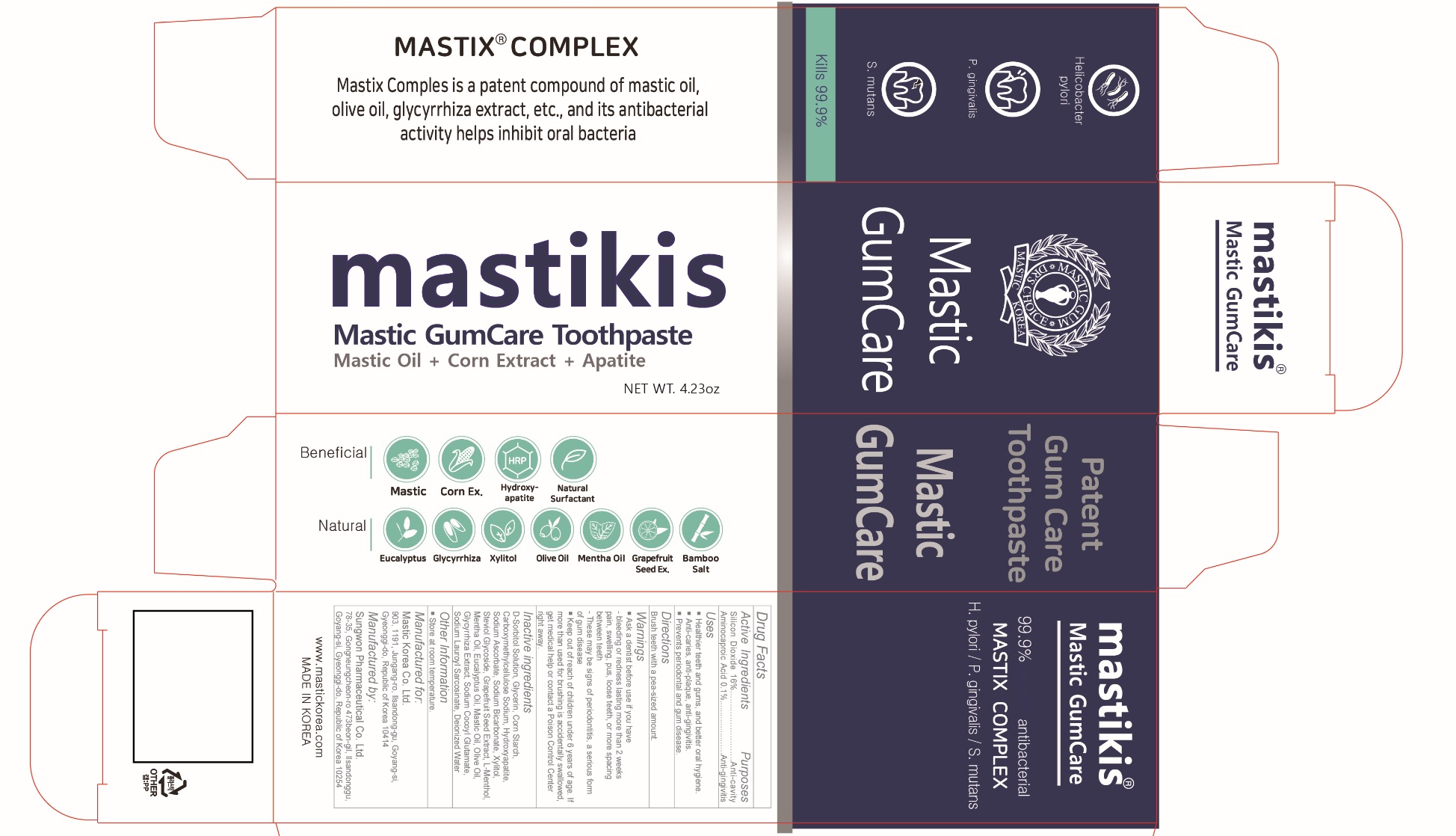 DRUG LABEL: Mastikis Mastic GumCare
NDC: 79814-009 | Form: PASTE, DENTIFRICE
Manufacturer: Mastic Korea.Co.Ltd
Category: otc | Type: HUMAN OTC DRUG LABEL
Date: 20210810

ACTIVE INGREDIENTS: SILICON DIOXIDE 16 g/100 g; AMINOCAPROIC ACID 0.1 g/100 g
INACTIVE INGREDIENTS: SORBITOL; GLYCERIN; CARBOXYMETHYLCELLULOSE SODIUM, UNSPECIFIED; STARCH, CORN; XYLITOL; STEVIOSIDE; SODIUM ASCORBATE; TRIBASIC CALCIUM PHOSPHATE; SODIUM BICARBONATE; LEVOMENTHOL; OLIVE OIL; EUCALYPTUS OIL; CITRUS PARADISI SEED; LICORICE; SODIUM COCOYL GLUTAMATE; SODIUM LAUROYL SARCOSINATE; WATER

79814-009_Mastikis Mastic GumCare Toothpaste

ACTIVE INGREDIENT

Silicon Dioxide 16%

Aminocaproic Acid 0.1%

INACTIVE INGREDIENT

D-Sorbitol Solution, Glycerin, Carboxymethylcellulose Sodium, Corn Starch, Xylitol, Steviol Glycoside, Sodium Ascorbate, Hydroxyapatite, Sodium Bicarbonate, L-Menthol, Mastic Oil, Mentha Oil, Olive Oil, Eucalyptus Oil, Grapefruit Seed Extract, Glycyrrhiza Extract, Sodium Cocoyl Glutamate, Sodium Lauroyl Sarcosinate, Deionized Water

Keep out of Reach of Children.

PURPOSE

Anti-cavity

Anti-gingivitis

WARNINGS

Ask a dentist before use if you have

- bleeding or redness lasting more than 2 weeks pain, swelling, pus, losse teeth, or more spacing between teeth

- These may be signs of periodontitis, a serious form of gum disease

INDICATIONS AND USAGE

- Healthier teeth and gums, and better oral hygiene.

- Anti-caries, anti-plaque, anti-gingivitis

- Prevents periodontal and gum disease

DOSAGE AND ADMINISTRATION

Brush teeth with a pea-sized amount